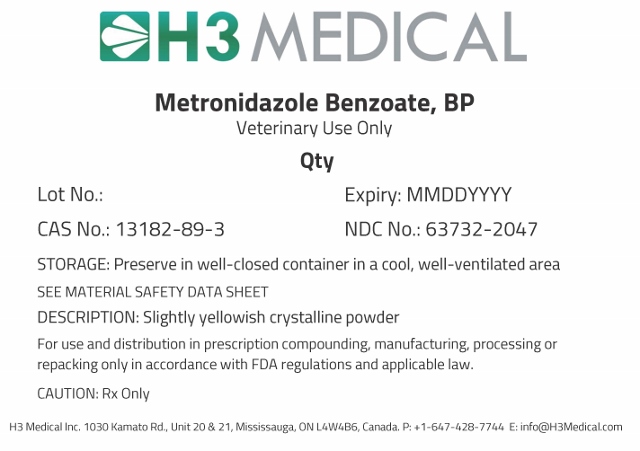 DRUG LABEL: Metronidazole Benzoate
NDC: 63732-2047 | Form: POWDER
Manufacturer: H3 Medical Inc.
Category: other | Type: BULK INGREDIENT
Date: 20190501

ACTIVE INGREDIENTS: METRONIDAZOLE BENZOATE 1 g/1 g

Metronidazole Benzoate